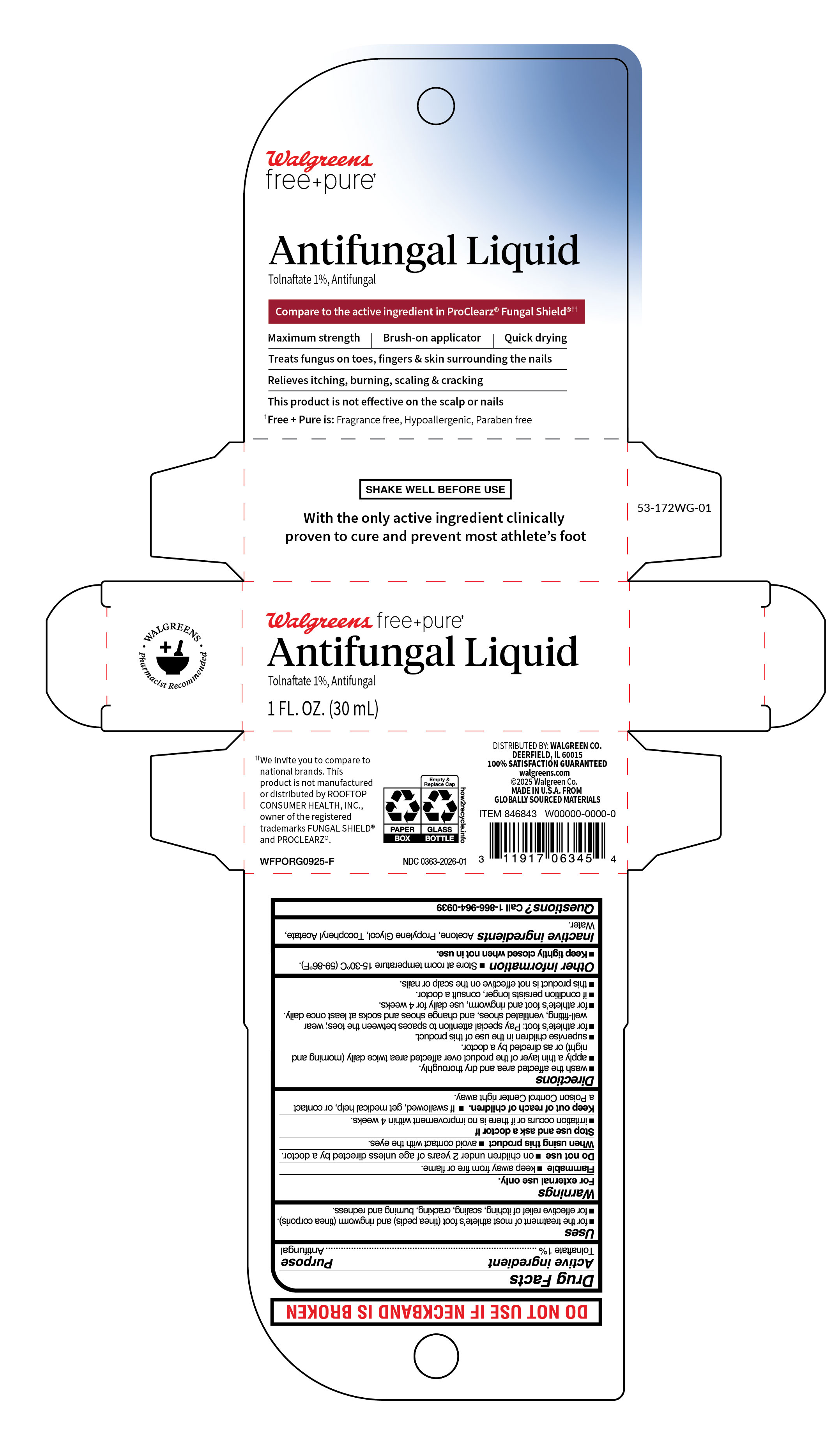 DRUG LABEL: Maximum Strength Antifungal Liquid
NDC: 0363-2026 | Form: LIQUID
Manufacturer: Walgreens Company
Category: otc | Type: HUMAN OTC DRUG LABEL
Date: 20251013

ACTIVE INGREDIENTS: TOLNAFTATE 10 mg/1 mL
INACTIVE INGREDIENTS: WATER; ALPHA-TOCOPHEROL ACETATE; ACETONE; PROPYLENE GLYCOL

Walgreens Maximum Strength Antifungal Liquid

Active ingredient

Tolnaftate 1%

Purpose

Antifungal

Uses

- For the treament of most athlete's foot (tinea pedis) and ring worm (tinea corporis).
- For effective relief of itching, scaling, cracking, burning, and redness.

Warnings

For external use only.

Flammable

- Keep away from fire or flame.

Do not use

on children under 2 years of age unless directed by a doctor.

When using this product

avoid contact with the eyes.

Stop use and consult a doctor if

- irritation occurs or if there is no improvement within 4 weeks.

Keep out of reach of children.

If swallowed, get medical help, or contact a Poison Control Center right away.

Directions

- wash the affected area and dry thoroughly.
- apply a thin layer of the product over affected area twice daily (morning and night) or as directed by a doctor.
- supervise children in the use of this product.
- for athlete's foot: Pay special attention to spaces between the toes; wear well-fitting, ventilated shoes, and change shoes and socks at least once daily.
- for athlete's foot and ringworm, use daily for 4 weeks.
- If condition persists longer, consult a doctor.
- this product is not effective on the scalp or nails.

Other information

- store at room temperature 15°-30°C (59° - 86°F).
- keep tightly closed when not in use.

Inactive ingredient

Acetone, Propylene Glycol, Tocopheryl Acetate, Water,

Questions?

Call 1-866-964-0939

RECENT MAJOR CHANGES

.

Principal Display Panel

Walgreens

free+pure

Antifungal Liquid

Tolnaftate 1%,Antifungal

Compare to the active ingredient in ProClearz Fungal Shield

Maximum strength | Brush-on applicator | Quick drying

Treats fungus on toes, fingers & skin surrounding the nails

Relieves itching, burning, scaling & cracking

This product is not effective on the scalp or nails

Free+Pure is: Fragrance free, Hypoallergenic, Paraben free

Walgreens free+pure

Antifungal Liquid

Tolnaftate 1%,Antifungal

1 FL. OZ. (30 mL)